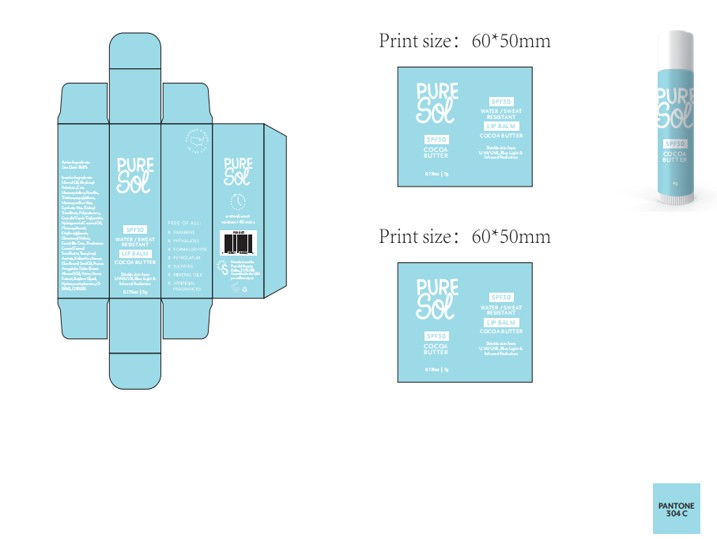 DRUG LABEL: PURE SOL SPF 30 LIP BALM CACOA BUTTER
NDC: 84090-005 | Form: STICK
Manufacturer: Brand 2022b LLC
Category: otc | Type: HUMAN OTC DRUG LABEL
Date: 20251004

ACTIVE INGREDIENTS: ZINC OXIDE 7.68 g/100 g
INACTIVE INGREDIENTS: MICROCRYSTALLINE WAX; BUTYLENE GLYCOL; HYDROXYACETOPHENONE; CANDELILLA CERA; ETHYLHEXYL PALMITATE; CI 15985; PEGZEREPOETIN ALFA; PARAFFIN; SYNTHETIC WAX (1900 MW); TRIDECYL TRIMELLITATE; .ALPHA.-TOCOPHEROL ACETATE; DIISOSTEARYL MALATE; HYDROGENATED COCONUT OIL; THEOBROMA CACAO (COCOA) SEED BUTTER; HYDROGENATED POLYISOBUTENE (450 MW); PRUNUS AMYGDALUS DULCIS (SWEET ALMOND) OIL; CI 19140; MINERAL OIL; TRIETHOXYCAPRYLYLSILANE; CAPRYLIC/CAPRIC TRIGLYCERIDE; PHENOXYETHANOL; ETHYLHEXYLGLYCERIN; HELIANTHUS ANNUUS (SUNFLOWER) SEED OIL; HONEY

84090-005-01. PURE SOL SPF 30 LIP BALM CACOA BUTTER—solid-5g

ACTIVE INGREDIENT

Zinc Oxide 7.68%

PURPOSE

-Helps prevent and temporarily chafed,chapped, cracked, or windburned skin and/or lips.
-helps prevent sunburn

Keep out of reach of children. If product is swallowed, get medical help or
contact a Poison Control Center right away.

Warnings
· For external use only
· Do not use on damaged or broken skin
· When using this product keep out of eyes. Rinse with water to remove

INDICATIONS AND USAGE

Apply liberally 15 minutes before sun exposure
- Reapply Liberally as often as necessary.
- Sun Protection Measures. Spending time in the sun increases your risk of skin
cancer and early skin aging. To decrease this risk, regularly use a sunscreen
with broad spectrum SPF of 15 or higher and other sun protection measures

INACTIVE INGREDIENT

MINERAL OIL
ETHYLHEXYL PALMITATE
CERA
PARAFFIN
TRIETHOXYCAPRYLYLSILANE
MICROCRYSTALLINE WAX
SYNTHETIC WAX
TRIDECYL TRIMELLITATE
POLYISOBUTENE
CAPRYLIC/CAPRIC TRIGLYCERIDE
HYDROGENATED COCONUT OIL
PHENOXYETHANOL
ETHYLHEXYLGLYCERIN
DIISOSTEARYL MALATE
CANDELILLA CERA
THEOBROMA CACAO (COCOA) SEED BUTTER
TOCOPHERYL ACETATE
HELIANTHUS ANNUUS (SUNFLOWER) SEED OIL
PRUNUS AMYGDALUS DULCIS (SWEET ALMOND) OIL
WATER
HONEY EXTRACT
BUTYLENE GLYCOL
HYDROXYACETOPHENONE
CI 19140
CI 15985

DOSAGE AND ADMINISTRATION

limit time in the sun, especially from 10 a.m. - 2 p.m.
- wear long-sleeve shirts, pants, hats, and sunglasses
- Reapply at least every 2 hours
- Use a water resistant sunscreen if swimming or sweating